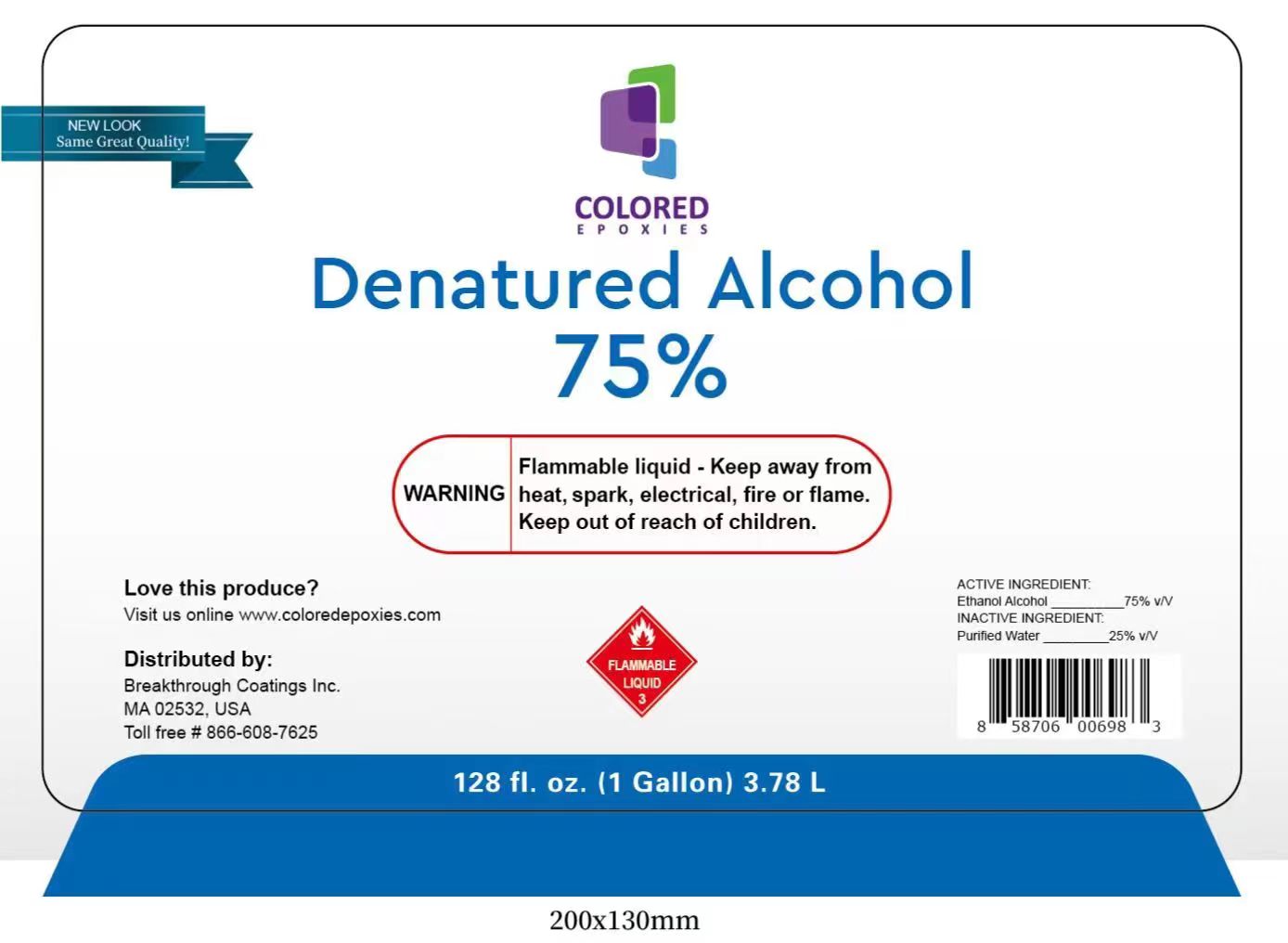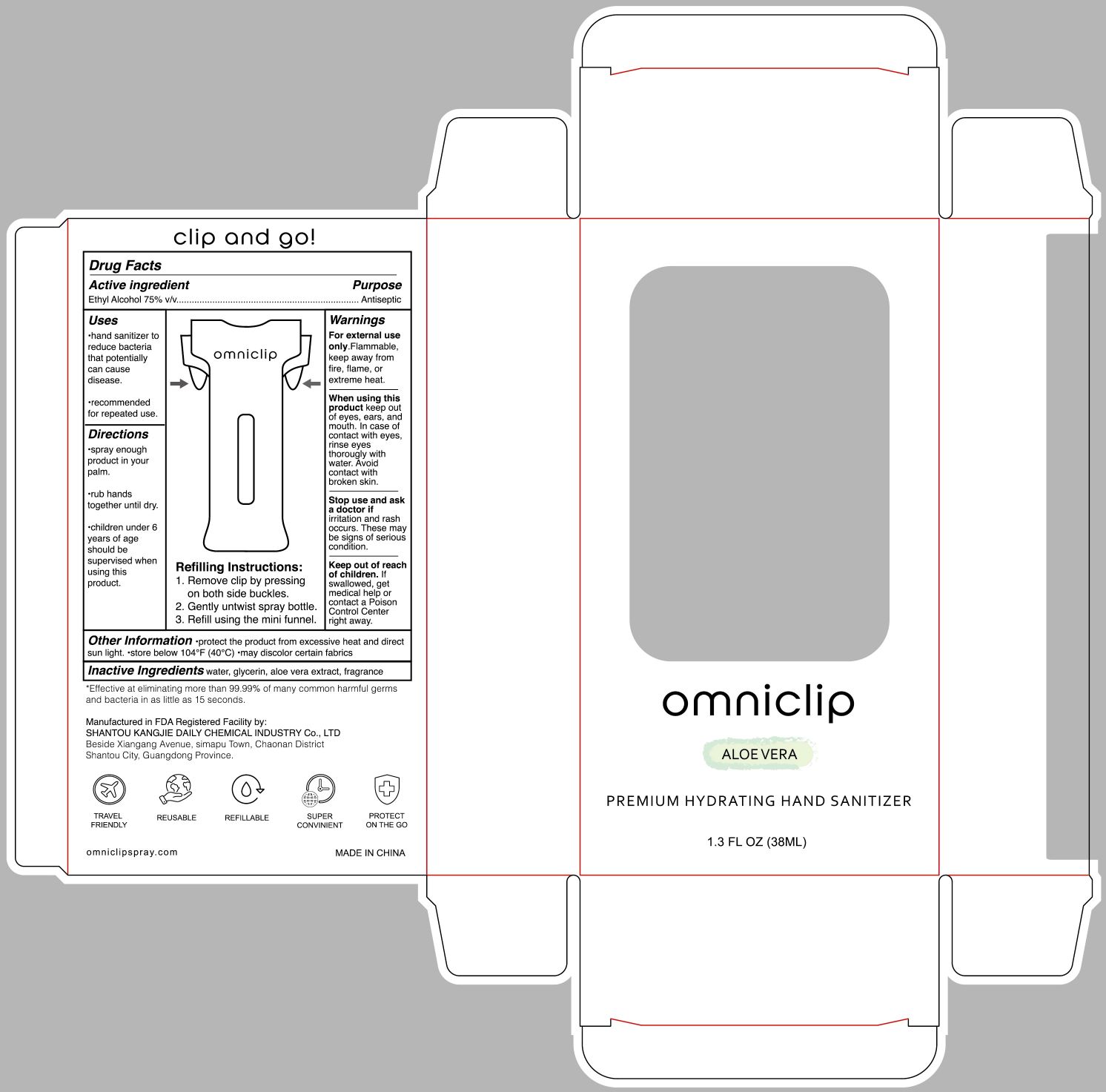 DRUG LABEL: Denatured Alcohol
NDC: 74047-003 | Form: LIQUID
Manufacturer: Shantou Kangjie Daily Chemical Industry Co.,Ltd
Category: otc | Type: HUMAN OTC DRUG LABEL
Date: 20230708

ACTIVE INGREDIENTS: ALCOHOL 75 mL/100 mL
INACTIVE INGREDIENTS: WATER

74047-003 Denatured Alcohol

ACTIVE INGREDIENT

Ethyl Alcohol 75% v/v

PURPOSE

Antimicrobial

INDICATIONS AND USAGE

Hand Sanitizer to help reduce bacteria on skin.

WARNING

Flammable liquid - Keep away from heat, spark, electrical, fire or flame.

Keep out of reach of children.

Do not use in the eyes. In case of contact, rinse eyes thoroughly with water.

When using this product,

Do not use in the eyes. In case of contact, rinse eyes thoroughly with water.

Stop use and ask doctor if irrtation or rash appears and lasts.

Keep out of reach of children. If swallowed, get medical help or contact a Poison Conter right away.

Stop use and ask doctor if irrtation or rash appears and lasts.

Keep out of reach of children. If swallowed, get medical help or contact a Poison Conter right away.

DOSAGE AND ADMINISTRATION

Place enough product in your palm to thoroughly spread on both hands.

Children under 6 years of age should be supervised when using this product.

INACTIVE INGREDIENT

Purified Water